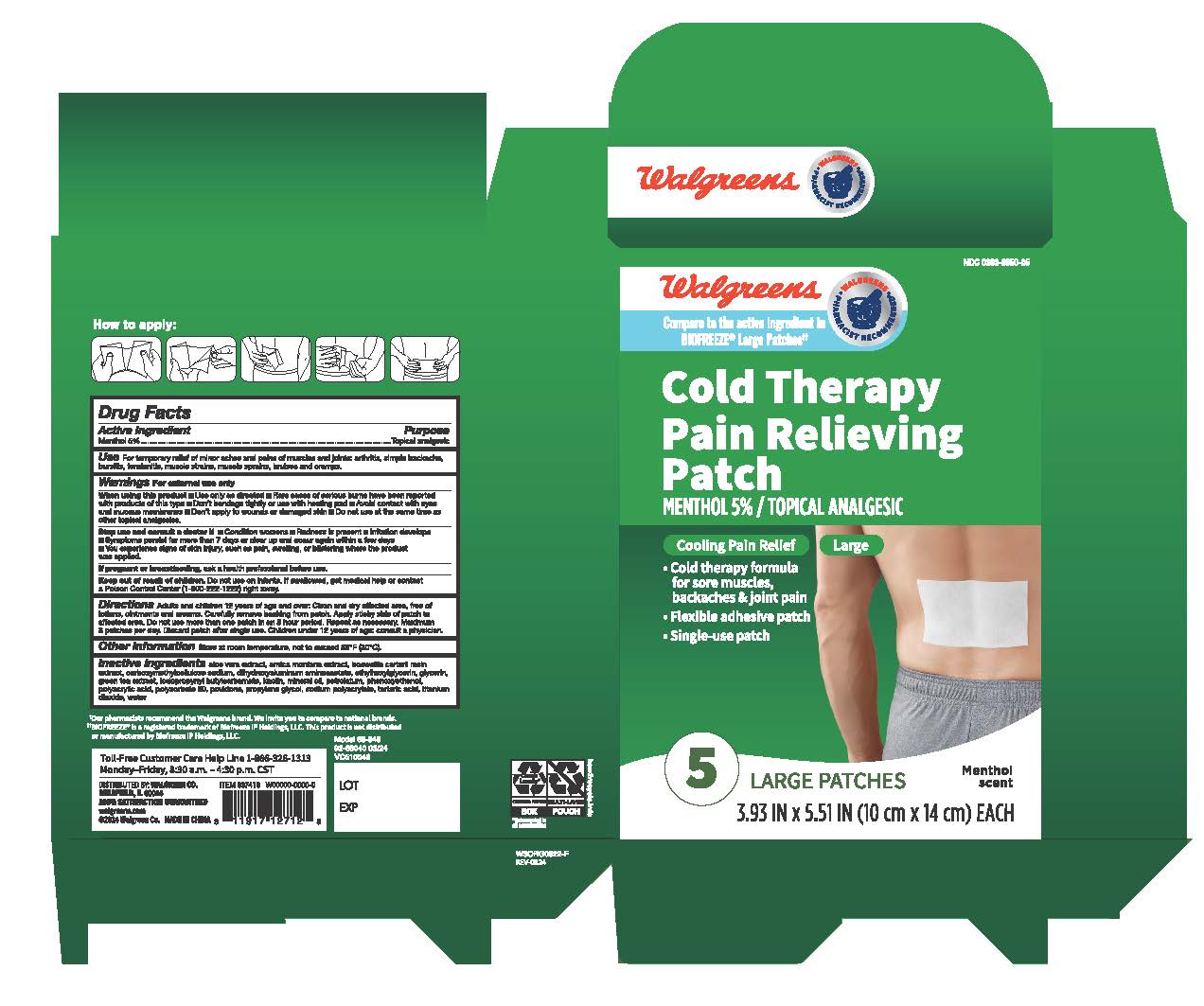 DRUG LABEL: Walgreens Cold Therapy Pain Relief Patch
NDC: 0363-9950 | Form: PATCH
Manufacturer: Walgreens Company
Category: otc | Type: HUMAN OTC DRUG LABEL
Date: 20240418

ACTIVE INGREDIENTS: MENTHOL 5 g/100 g
INACTIVE INGREDIENTS: GREEN TEA LEAF; IODOPROPYNYL BUTYLCARBAMATE; MINERAL OIL; POLYACRYLIC ACID (450000 MW); ARNICA MONTANA FLOWER; GLYCERIN; POVIDONE; TITANIUM DIOXIDE; FRANKINCENSE; PETROLATUM; TARTARIC ACID; WATER; DIHYDROXYALUMINUM AMINOACETATE; ETHYLHEXYLGLYCERIN; PHENOXYETHANOL; CARBOXYMETHYLCELLULOSE SODIUM; KAOLIN; PROPYLENE GLYCOL; SODIUM POLYACRYLATE (2500000 MW); POLYSORBATE 80; ALOE VERA LEAF

Walgreens Cold Therapy Pain Relief Patch

Active Ingredient

Menthol 5%

Purpose

Topical Analgesic

Uses

For temporary relief of minor aches and pains of muscles and joints:

arthritis
simple backache
bursitis
tendonitis
muscle strains
muscle sprains
bruises
and cramps

Warnings

For external use only

When using this product

- use only as directed
- rare cases of serious burns have been reported with products of this type
- do not bandage tightly or use with heating pad or device
- avoid contact with the eyes or on mucous membranes
- do not apply to wounds or damaged skin
- do not use at the same time as other topical analgesics

Stop Use and ask your doctor

- condition worsens
- Redness is present
- Irritation develops
- Symptoms persist for more than 7 days or clear up and occur again within a few days
- you experience signs of skin injury, such as pain, swelling, or blistering where the product was applied

If pregnant or breast-feeding, ask a health professional before use.

Keep out of reach of children. Do not use on infants. If swallowed, get medical help or contact a Poison Control Center (1-800-222-1222) right away.

Directions

adults and children 12 years of age and over: Carefully remove backing from patch. Apply sticky side of patch to affected area. Wear one patch up to 8 hours. Repeat as necessary, but no more than 3 times daily. Discard patch after single use. Reseal pouch after opening. Children under 12 years of age: consult a physician.

Other information

store at room temperature, not to exceed 86°F (30°C)

Inactive Ingredients

aloe vera extract, arnica montana extract, boswellia carterii resin extract, carboxymethylcellulose sodium, dihydroxyaluminum aminoacetate, ethylhexylglycerin, glycerin, green tea extract, iodopropynyl butylcarbamate, kaolin, mineral oil, petrolatum, phenoxyethanol, polyacrylic acid, polysorbate 80, povidone, propylene glycol, sodium polyacrylate, tartaric acid, titanium dioxide, water

Questions or Comments

1-866-326-1313